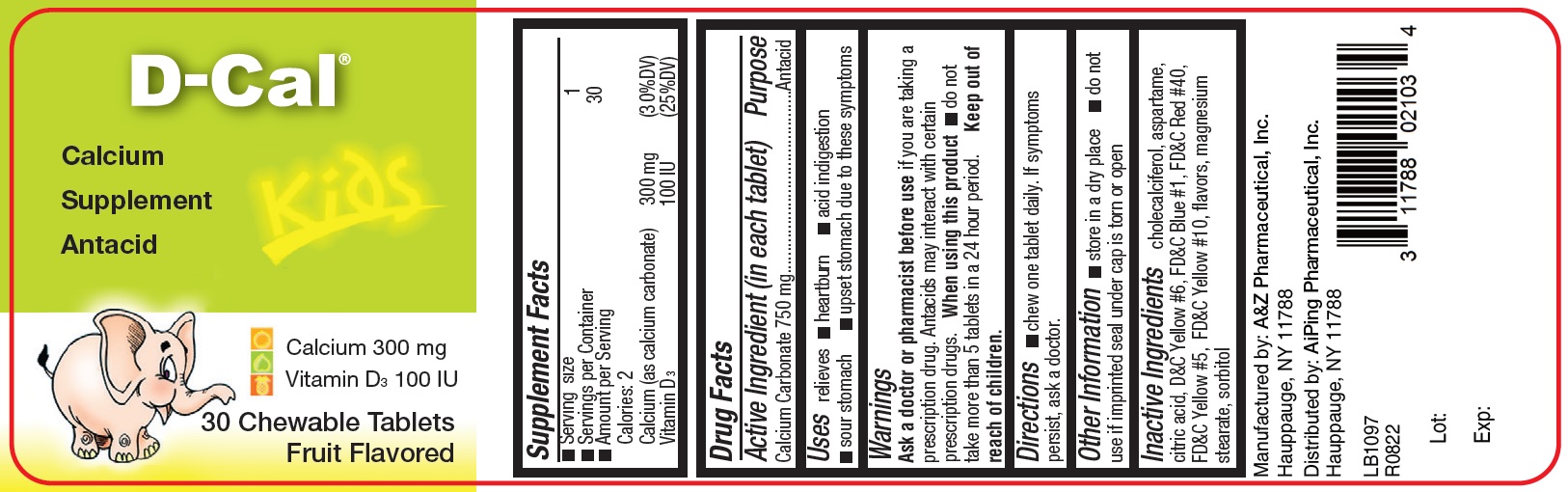 DRUG LABEL: D-Cal Kids
NDC: 11788-021 | Form: TABLET, CHEWABLE
Manufacturer: AiPing Pharmaceutical, Inc.
Category: otc | Type: HUMAN OTC DRUG LABEL
Date: 20250828

ACTIVE INGREDIENTS: CALCIUM CARBONATE 750 mg/1 1
INACTIVE INGREDIENTS: CHOLECALCIFEROL; ASPARTAME; CITRIC ACID MONOHYDRATE; FD&C BLUE NO. 1; FD&C RED NO. 40; FD&C YELLOW NO. 5; FD&C YELLOW NO. 6; D&C YELLOW NO. 10; MAGNESIUM STEARATE; SORBITOL

D-Cal Kids

ACTIVE INGREDIENTS

Calcium Carbonate 750 mg

PURPOSES

Antacid

USES

Relieves

- heartburn
- acid indigestion
- sour stomach
- upset stomach due to these symptoms

WARNINGS

Ask a doctor or pharmacist before use if you are taking a prescription drug. Antacids may interact with certain prescription drugs. When using this product do not take more than 5 tablets in a 24 hour period. Keep out of reach of children.

Directions

- chew one tablet daily. If symptoms persist, ask a doctor.

Other Information

- store in a dry place
- do not use if imprinted seal under cap is torn or open

Inactive ingredients

cholecalciferol, aspartame, citric acid, D&C Yellow #6, FD&C Blue #1, FD&C Red #40, FD&C Yellow #5, FD&C Yellow #10, flavors, magnesium stearate, sorbitol